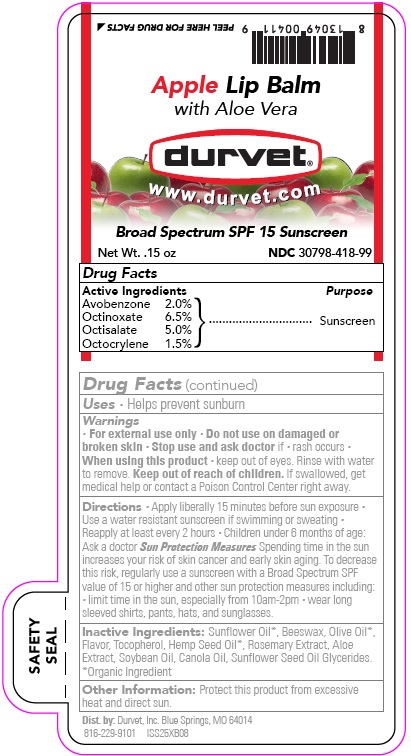 DRUG LABEL: Apple Lip Balm with Aloe Vera
NDC: 30798-418 | Form: STICK
Manufacturer: Durvet, Inc.
Category: otc | Type: HUMAN OTC DRUG LABEL
Date: 20251006

ACTIVE INGREDIENTS: AVOBENZONE 0.085 g/4.25 g; OCTINOXATE 0.28 g/4.25 g; OCTISALATE 0.21 g/4.25 g; OCTOCRYLENE 0.06 g/4.25 g
INACTIVE INGREDIENTS: SUNFLOWER OIL; BEESWAX; OLIVE OIL; TOCOPHEROL; CANNABIS SATIVA SEED OIL; ROSEMARY; ALOE; SOYBEAN OIL; CANOLA OIL; SUNFLOWER OIL MONO/DIGLYCERIDES

Broad Spectrum SPF 15 Sunscreen Lip Balm

Drug Facts

Active Ingredients:

Avobenzone 2.0%

Octinoxate 6.5%

Octisalate 5.0%

Octocrylene 1.5%

Purpose

Sunscreen

INDICATIONS AND USAGE

Uses • Helps prevent sunburn

WARNINGS

Drug Facts (continued)

Warnings

•For external use only.

•Do not use on damaged or broken skin

•Stop use and ask doctor if •rash occurs•

When using this product keep out of eyes. Rinse with water to remove.

Keep out of reach of children. If swallowed, get medical help or contact a Poison Control Center right away.

DOSAGE AND ADMINISTRATION

Directions: •Apply liberally 15 mintues before sun exposure. •Use a water resistant sunscreen if swimming or sweating. •Reapply at least every 2 hours. •Children under 6 months of age: Ask a doctor. Sun Protection Measures Spending time in the sun increases
your risk of skin cancer and early skin aging. To decrease this risk, regularly
use a sunscreen with a Broad Spectrum SPF value of 15 or higher and other
sun protection measures including: • limit time in the sun, especially from
10a.m. - 2p.m. • wear long sleeved shirts, pants, hats, and sunglasses.

Inactive Ingredients: Sunflower Oil*, Beeswax, Olive Oil*,
Flavor, Tocopherol, Hemp Seed Oil*, Rosemary Extract, Aloe
Extract, Soybean Oil, Canola Oil, Sunflower Seed Oil Glycerides.
*Organic Ingredient

Other Information: Protect this product from excessive heat and direct sun.

PACKAGE LABEL

Apple Lip Balm

With Aloe Vera

Durvet®

www.durvet.com

Broad Spectrum SPF 15 Sunscreen

Net Wt. .15 oz NDC 30798-418-99

Dist. by: Durvet, Inc. Blue Springs, MO 64014

816-229-9101 lSS25XB08

RES